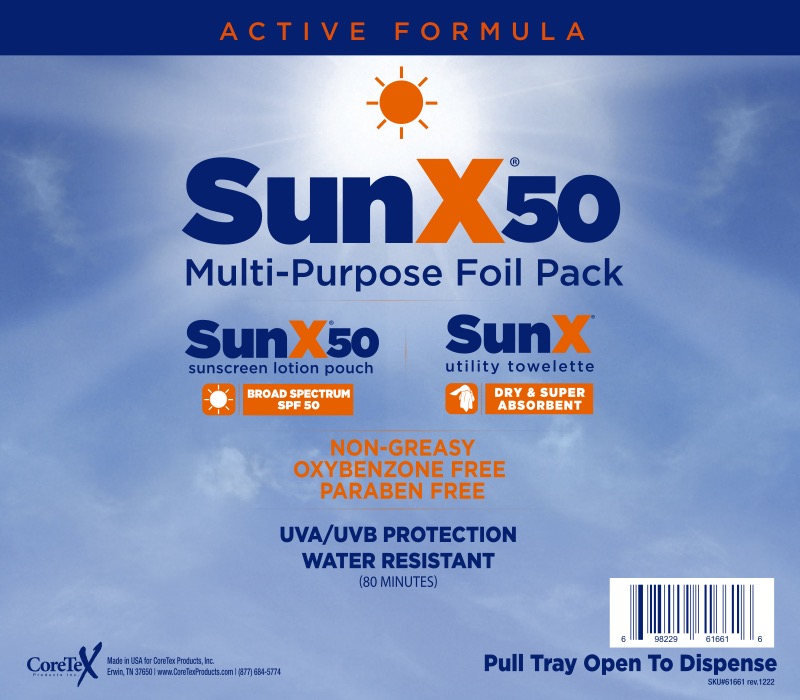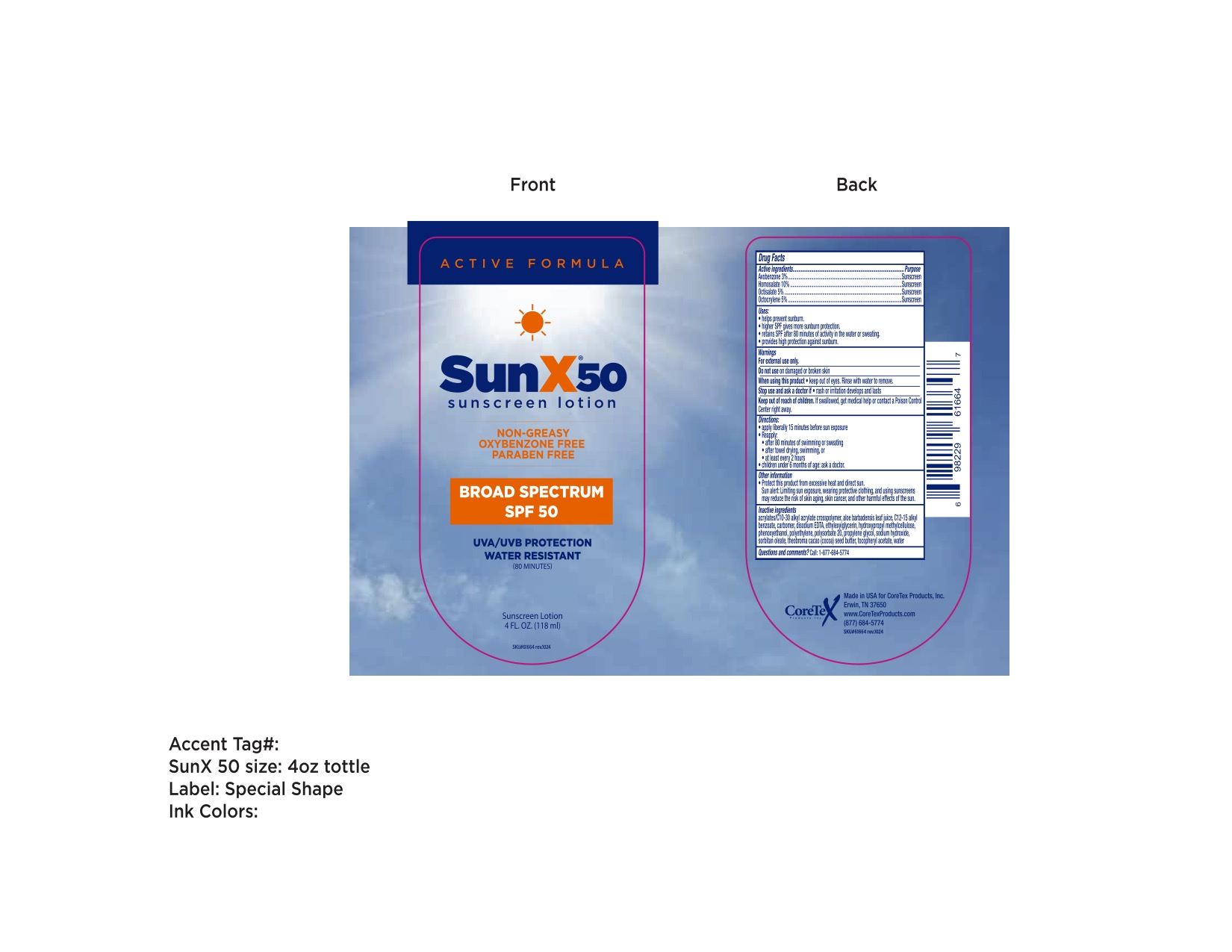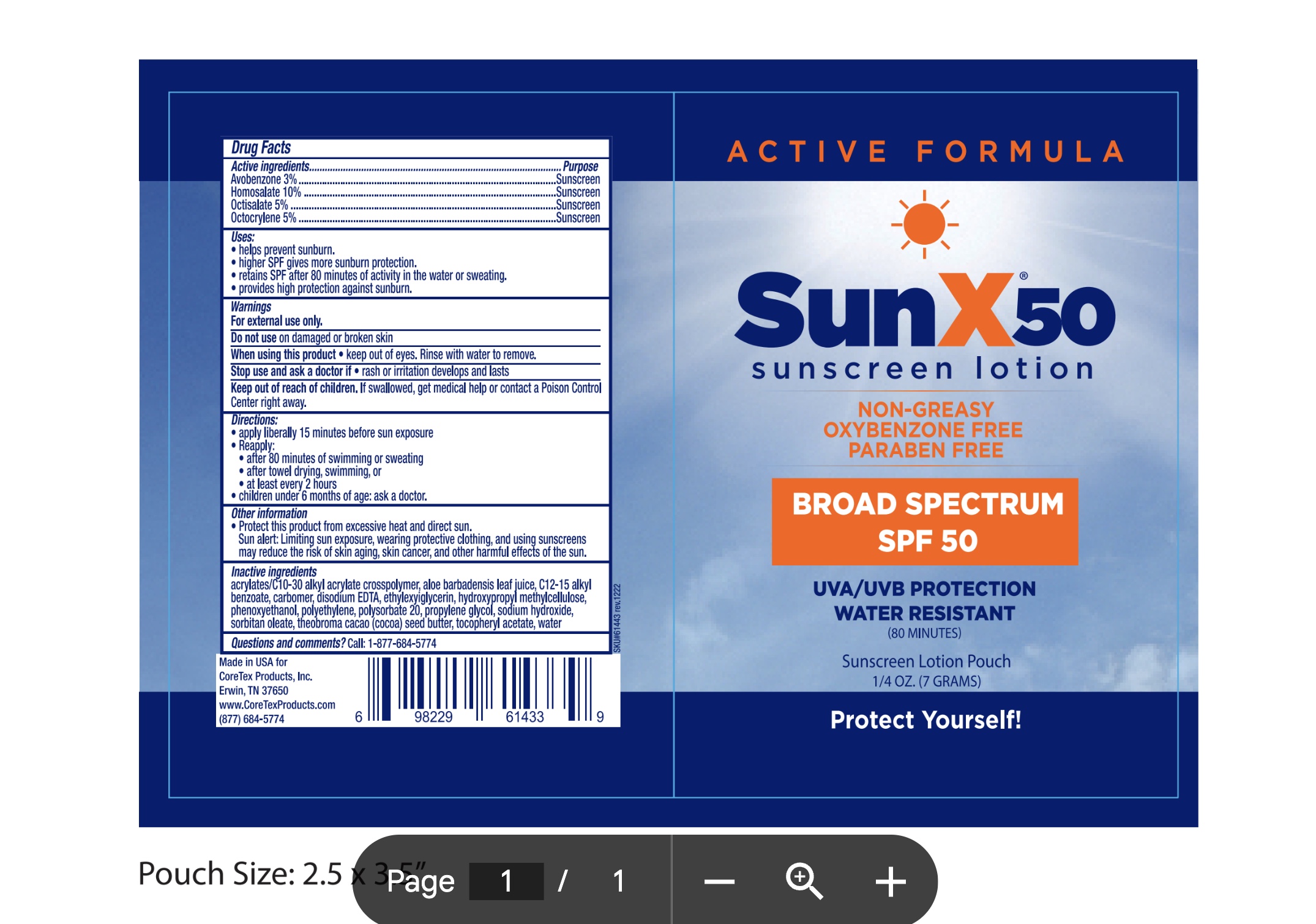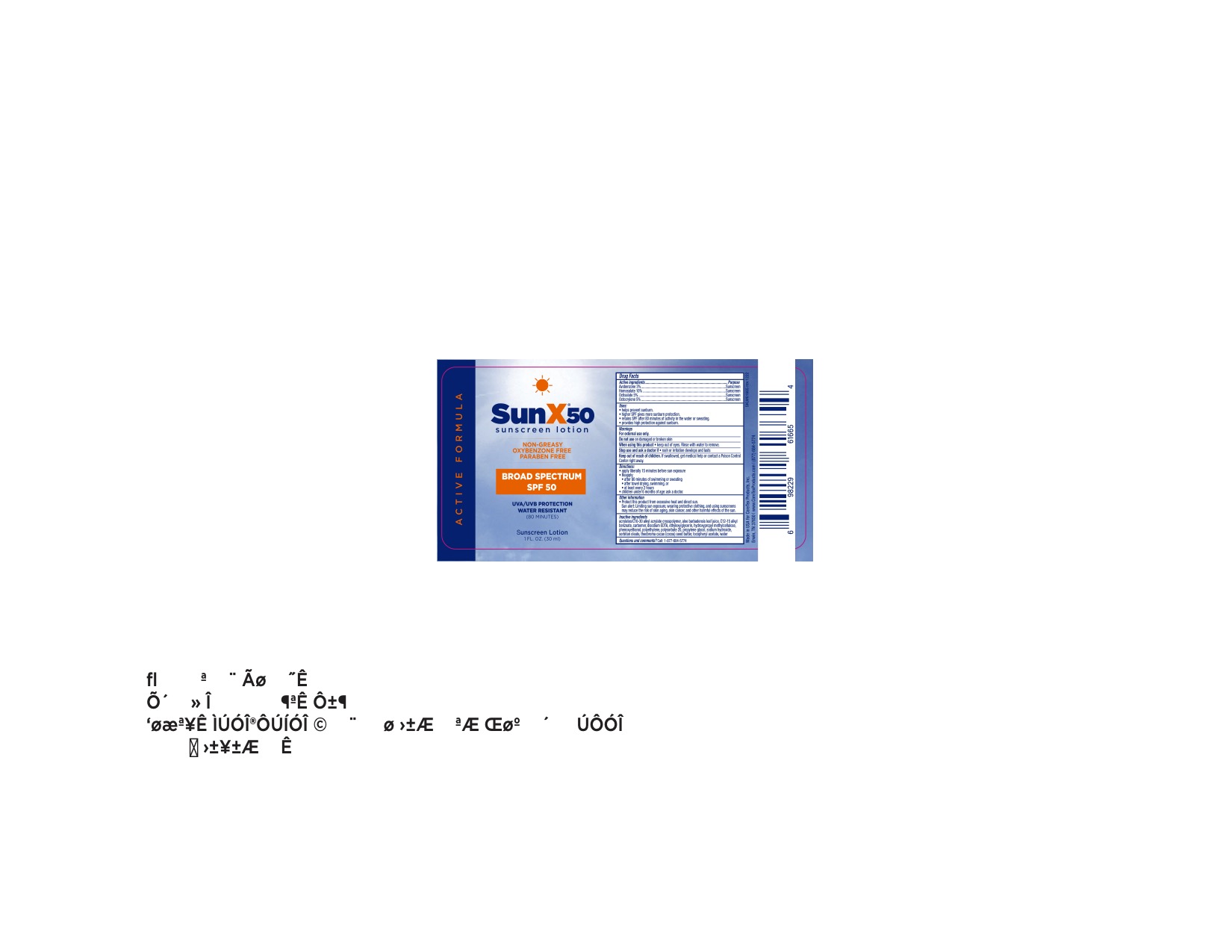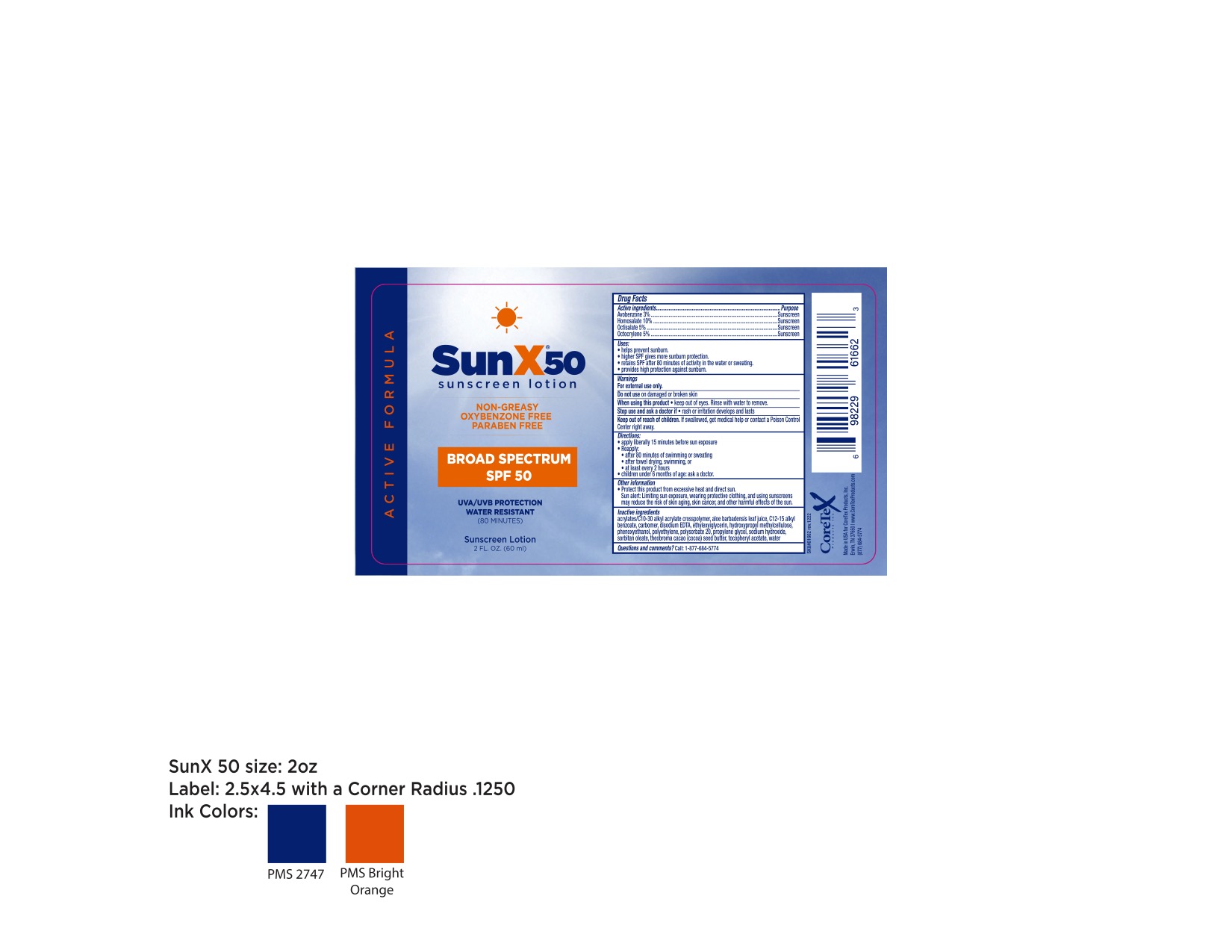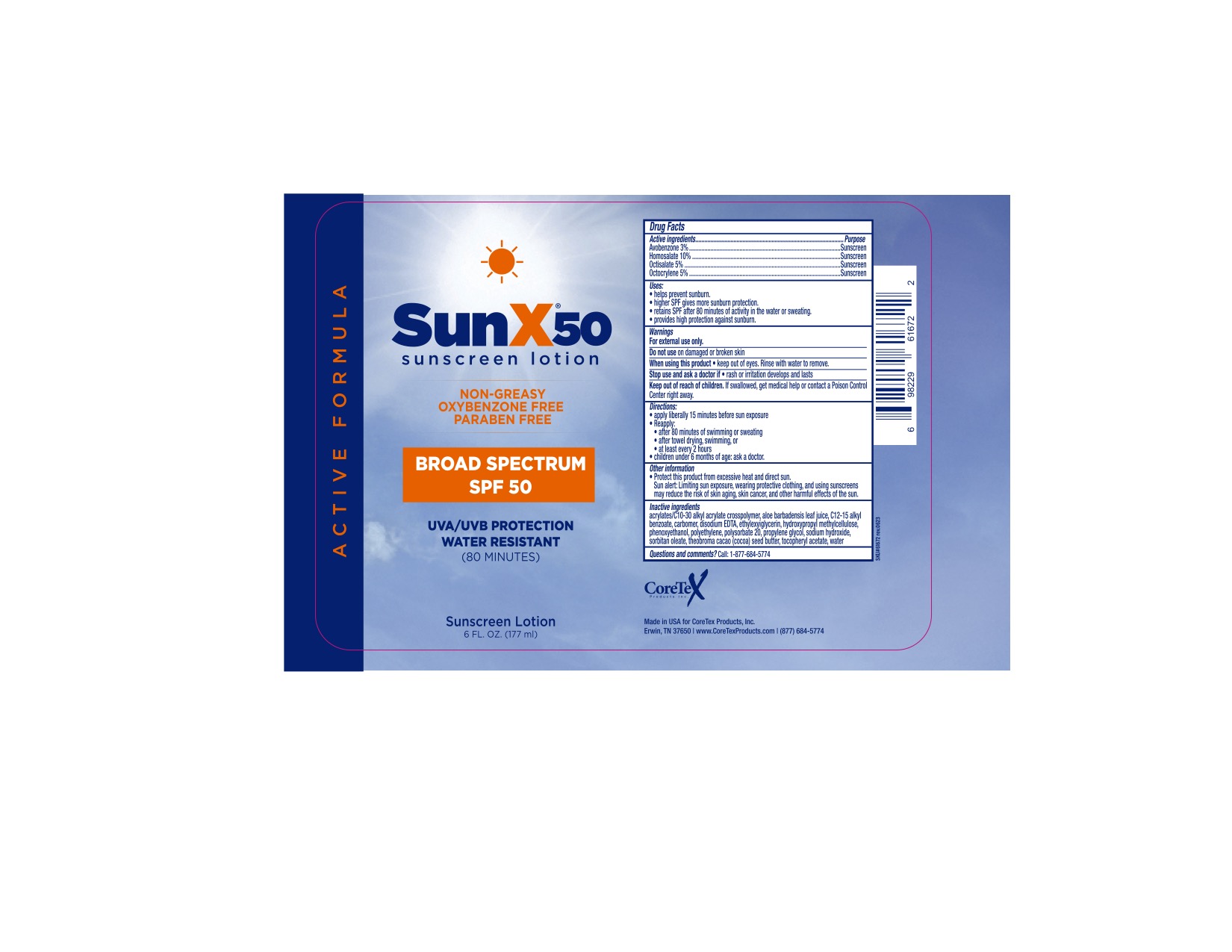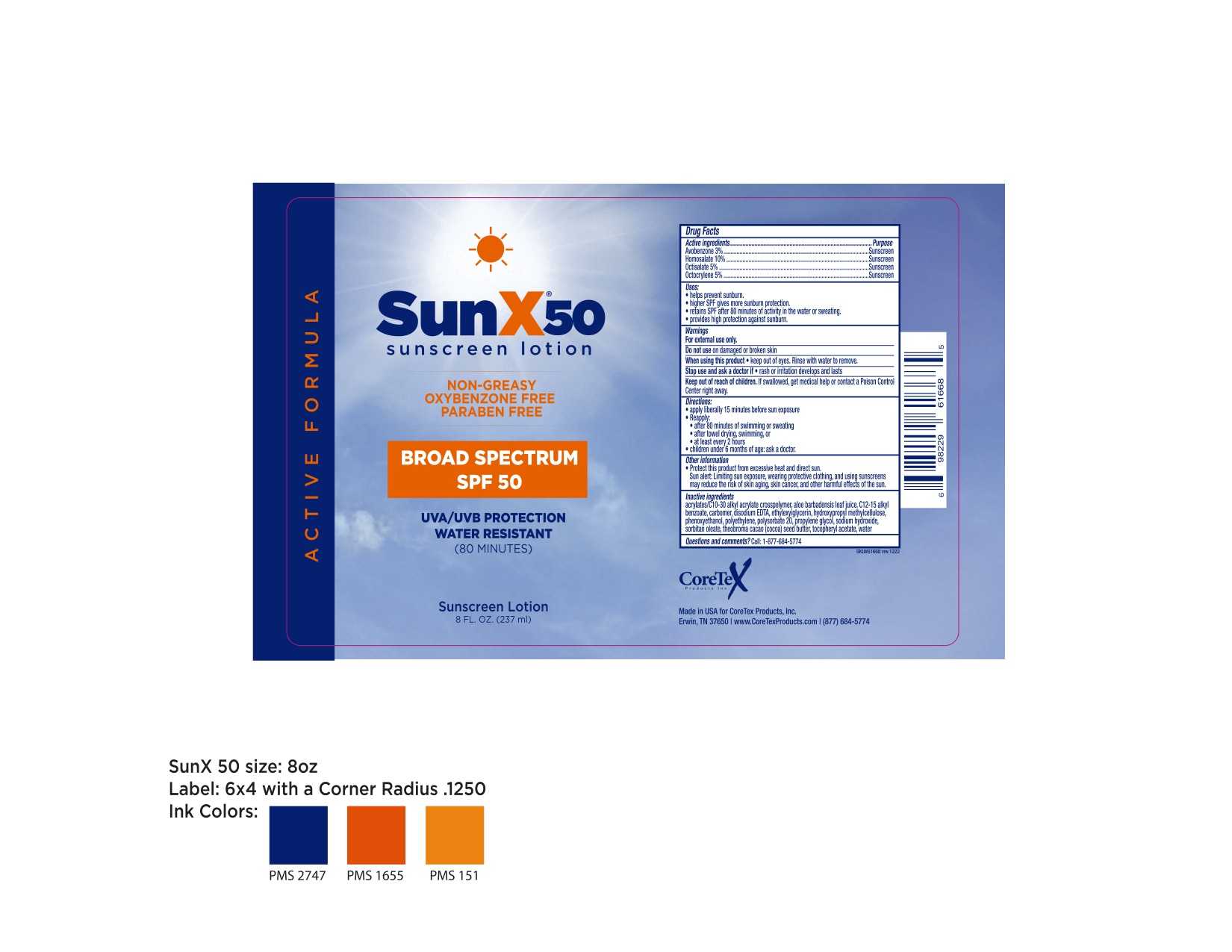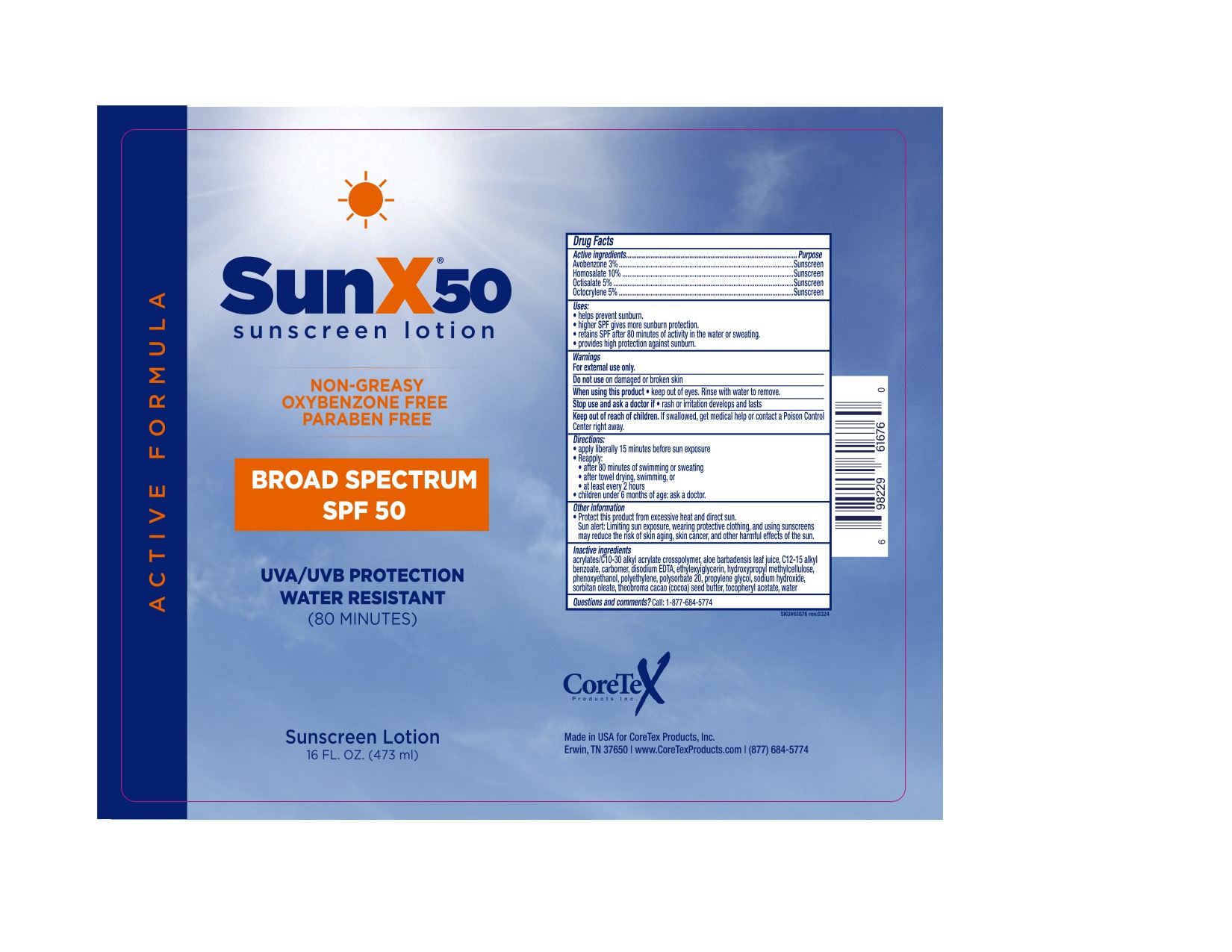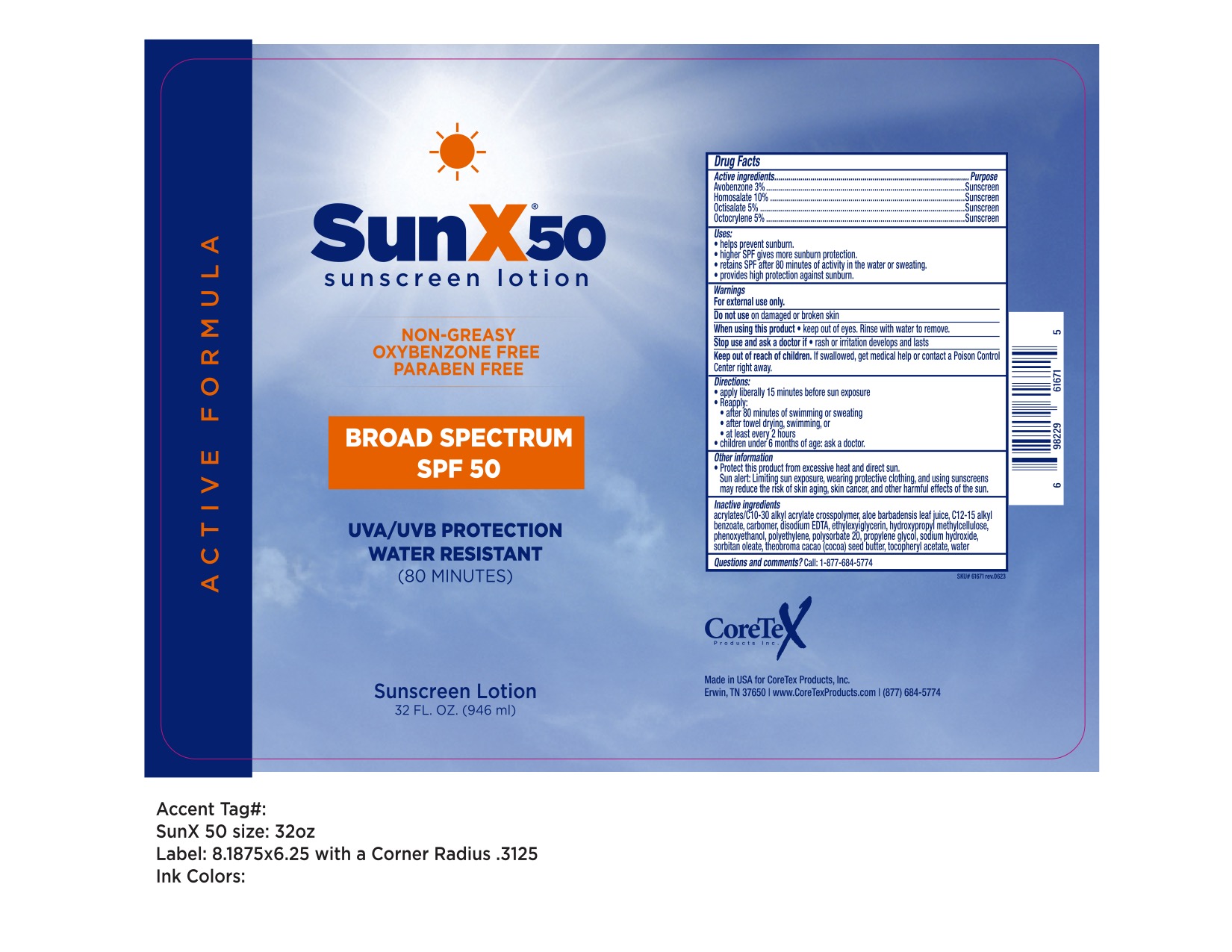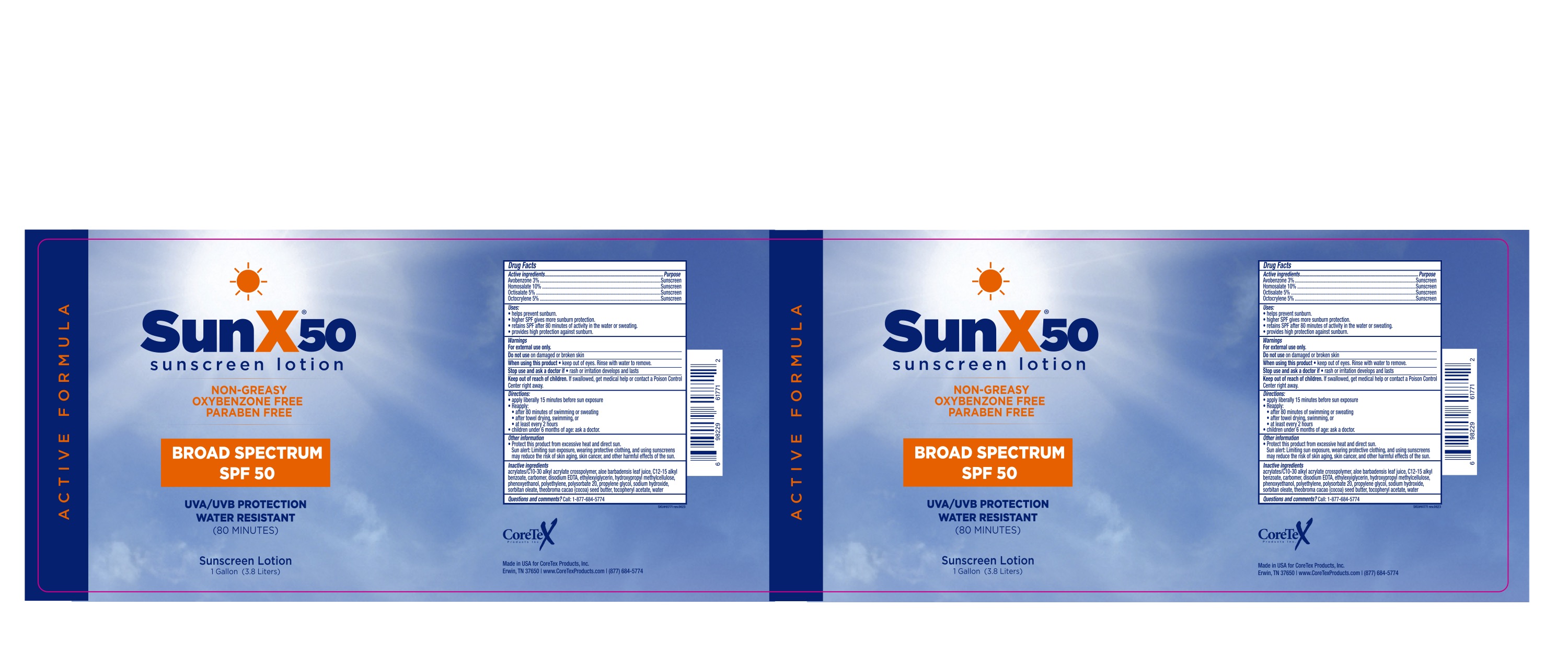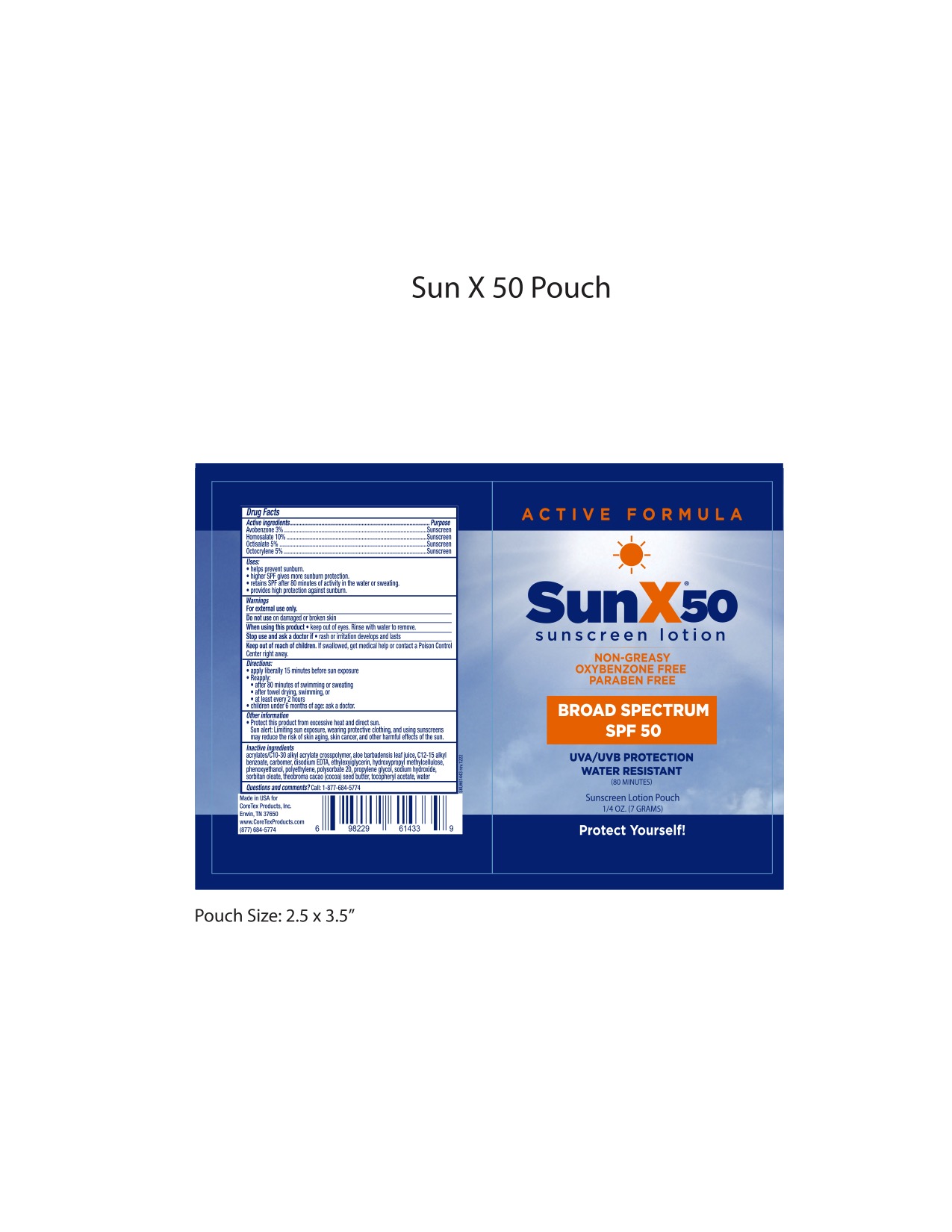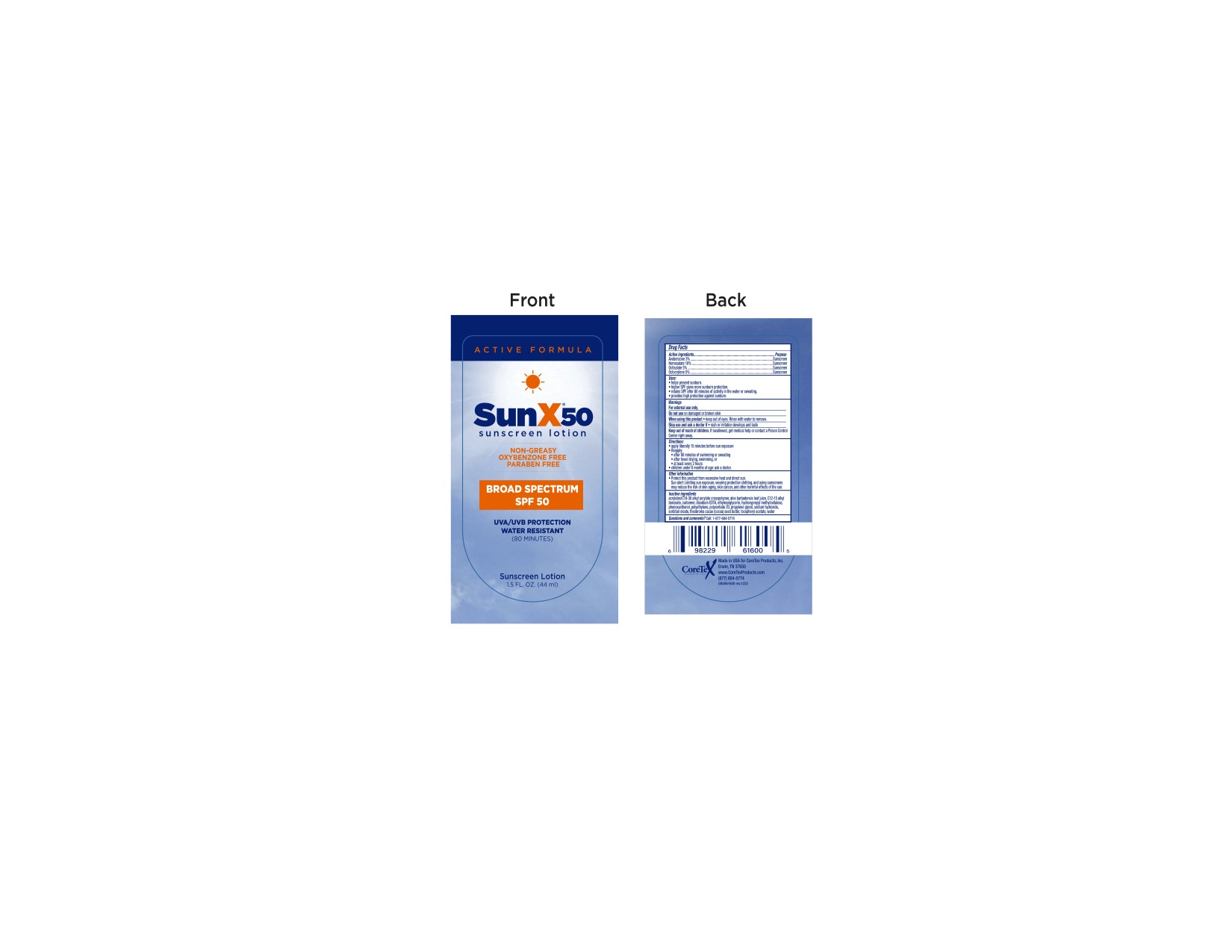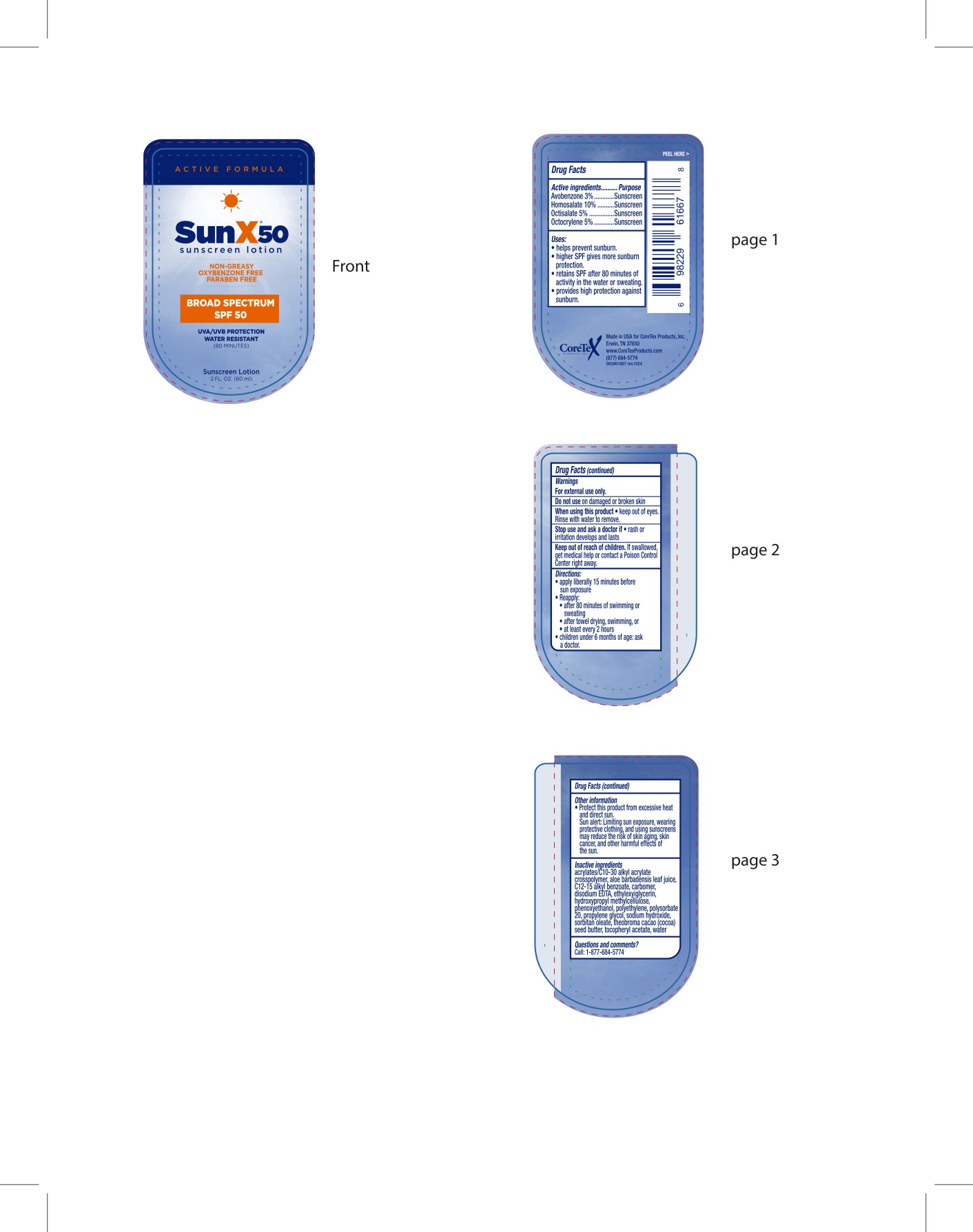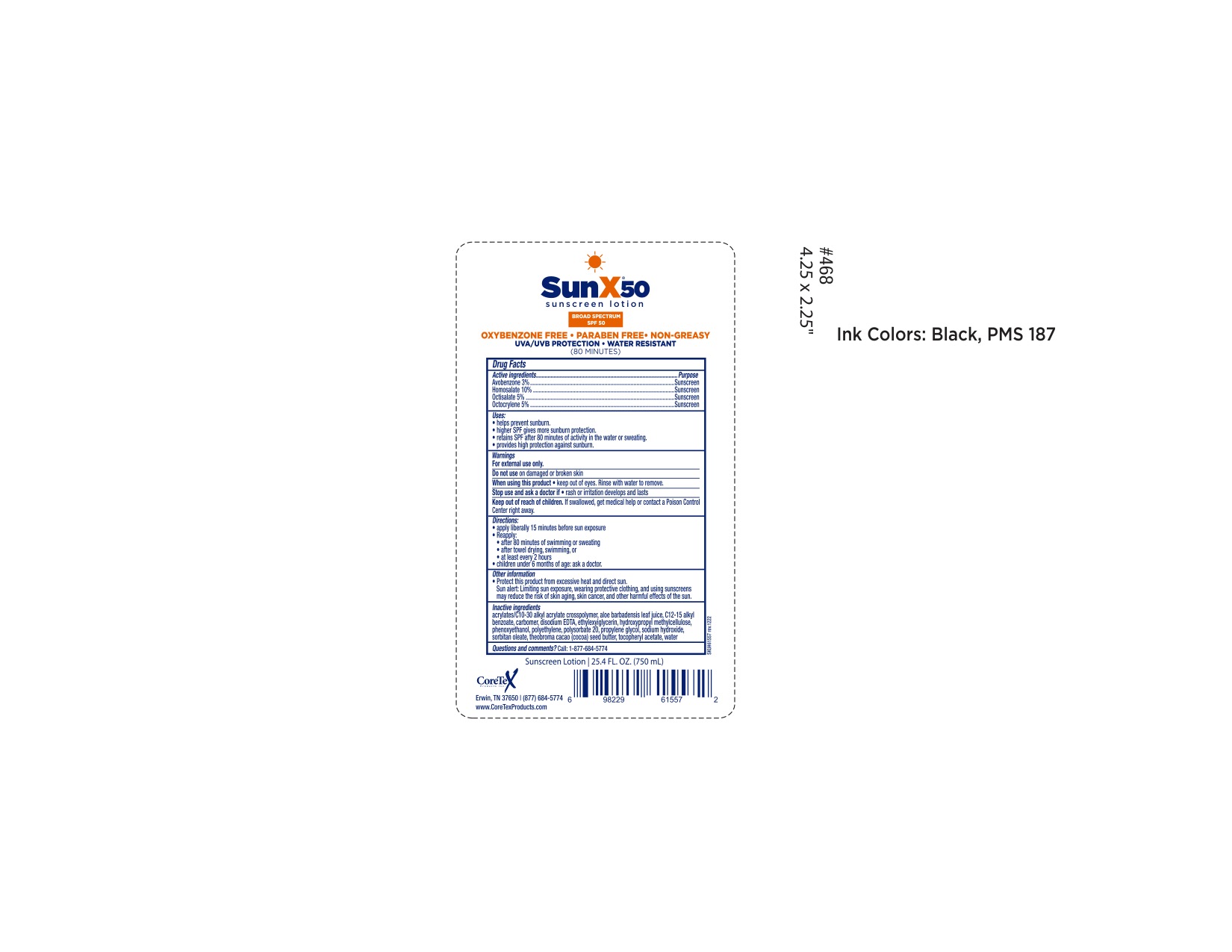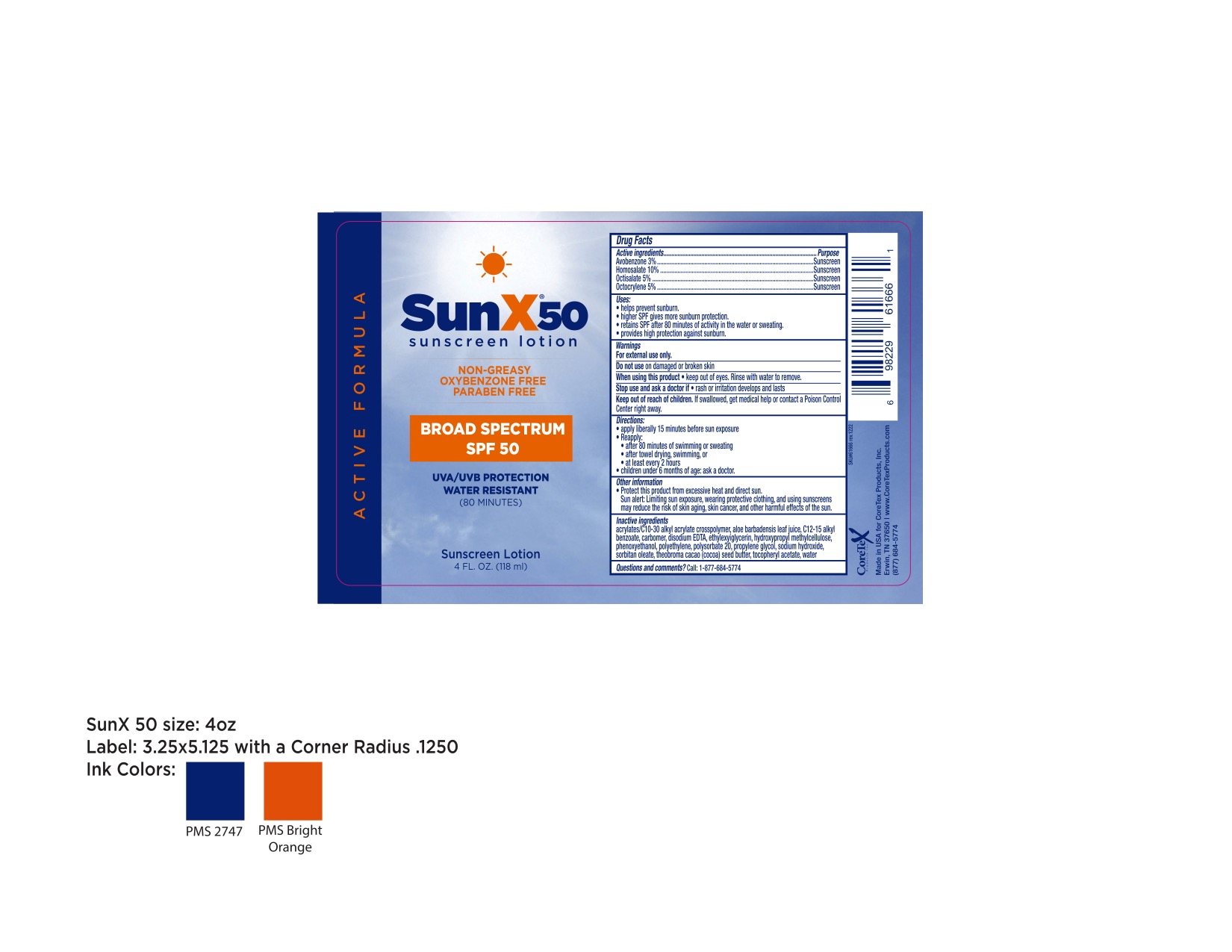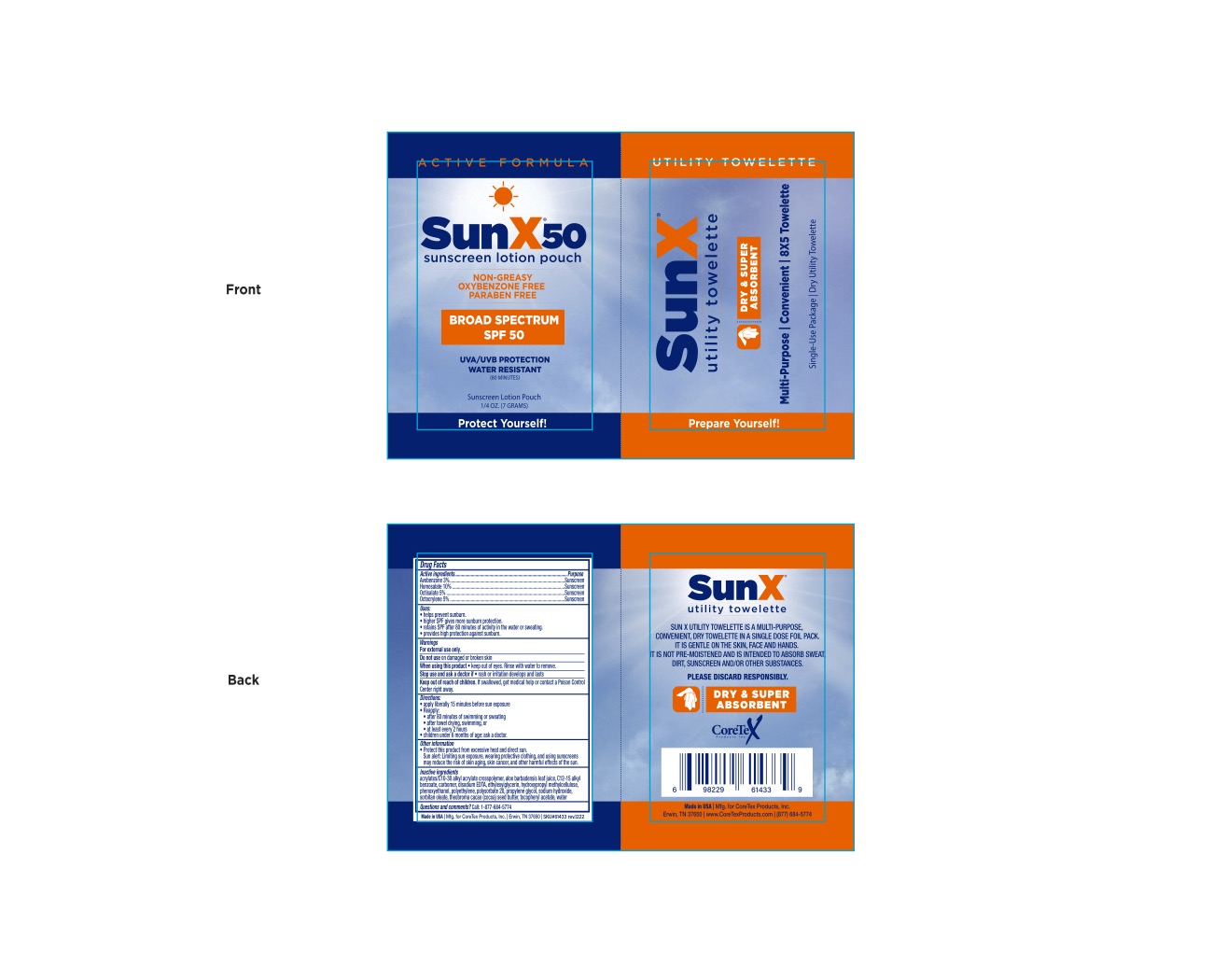 DRUG LABEL: CorTex SunX 50 Thick
NDC: 65753-602 | Form: LOTION
Manufacturer: CoreTex Products Inc
Category: otc | Type: HUMAN OTC DRUG LABEL
Date: 20250206

ACTIVE INGREDIENTS: HOMOSALATE 10 g/100 g; OCTOCRYLENE 5 g/100 g; OCTISALATE 5 g/100 g; AVOBENZONE 3 g/100 g
INACTIVE INGREDIENTS: PHENOXYETHANOL; PROPYLENE GLYCOL; ETHYLHEXYLGLYCERIN; WATER; THEOBROMA CACAO WHOLE; SODIUM HYDROXIDE; C12-20 ALKYL BENZOATE; DISODIUM EDTA-COPPER; METHYLCELLULOSE, UNSPECIFIED; ACRYLATES CROSSPOLYMER-6; .ALPHA.-TOCOPHEROL ACETATE; PEG-6 SORBITAN OLEATE; ALOE VERA LEAF; CARBOMER HOMOPOLYMER, UNSPECIFIED TYPE; MEDIUM DENSITY POLYETHYLENE; POLYSORBATE 20

CoreTex SunX 50 Thick
65753-604
and Multipack
65753-602

Active Ingredients:

Avobenzone...3%

Homosalate...10%

Octisalate...5%

Octocrylene...5%

Purpose

Sunscreen

Sunscreen

Sunscreen

Sunscreen

Uses:

- helps prevent sunburn.
- higher SPF gives more sunburn protection.
- retains SPF after 80 minutes of activity in the water or sweating.
- provides high protection against sunburn.

Warnings

For external use only.

Do not use

- on damaged or broken skin

When using this product

- keep out of eyes. Rinse with water to remove

Stop use and ask a doctor if

- rash or irritation develops and lasts

Keep out of reach of children

If swallowed, get medical help or contact a Poison Control Center right away.

Directions:

- apply liberally 15 minutes before sun exposure.

- Reapply:
- after 80 minutes of swimming or sweating
- after towel drying, swimming, or
- at least every 2 hours

- Children under 6 months of age: ask a doctor.

Other Information:

- Protect this product from excessive heat and direct sun.

Sun alert: Limiting sun exposure, wearing protective clothing, and using sunscreens may reduce the risk of skin aging, skin cancer, and other harmful effects of the sun.

Inactive ingredients

acrylates/C10-30 alkyl acrylate crosspolymer, aloe barbedensis leaf juice, C12-15 alkyl benzoate,carbomer, disodium EDTA, ethylhexylglycerin, hydroxypropyl methylcellulose, phenoxyethanol,polyethylene, polysorbate 20, propylene glycol, sodium hydroxide, sorbitan oleate, theobroma cacao (cocoa) seed butter, tocopheryl acetate, water.

Questions?

Call: 1-877-684-5774